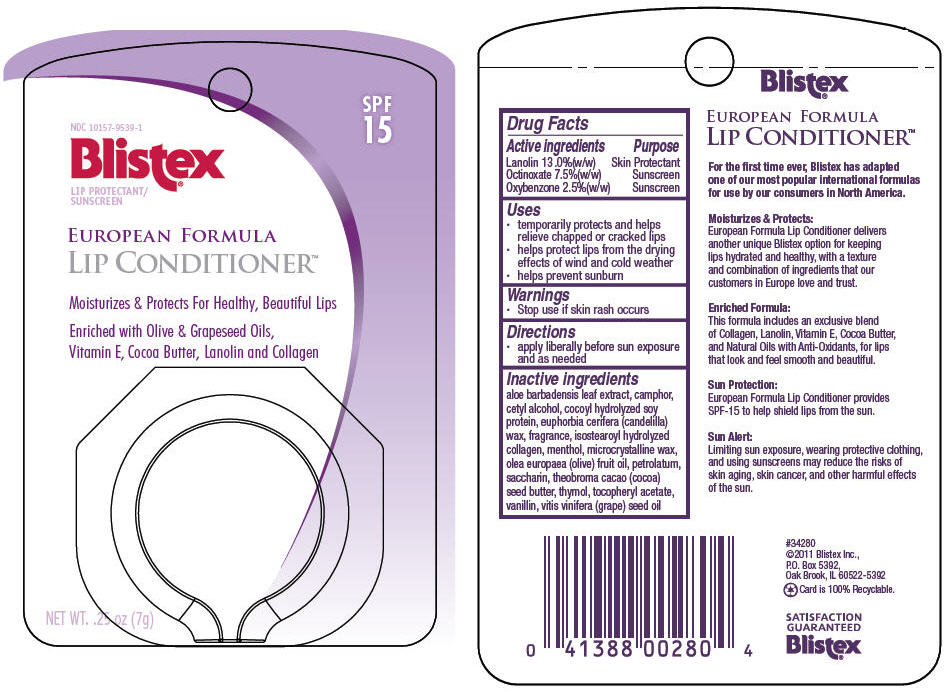 DRUG LABEL: Blistex 
NDC: 10157-9539 | Form: PASTE
Manufacturer: Blistex Inc.
Category: otc | Type: HUMAN OTC DRUG LABEL
Date: 20120316

ACTIVE INGREDIENTS: Lanolin 13 g/100 g; Octinoxate 7.5 g/100 g; Oxybenzone 2.5 g/100 g
INACTIVE INGREDIENTS: aloe vera leaf; camphor (synthetic); cetyl alcohol; candelilla wax; menthol; microcrystalline wax; olive oil; petrolatum; saccharin; cocoa butter; thymol; .alpha.-tocopherol acetate; vanillin; grape seed oil

Blistex®
European Formula
Lip Conditioner™

Drug Facts

ACTIVE INGREDIENT

Active ingredients | Purpose
Lanolin 13 .0%(w/w) | Skin Protectant
Octinoxate 7.5%(w/w) | Sunscreen
Oxybenzone 2.5%(w/w) | Sunscreen

Uses

- temporarily protects and helps relieve chapped or cracked lips
- helps protect lips from the drying effects of wind and cold weather
- helps prevent sunburn

Warnings

- Stop use if skin rash occurs

Directions

- apply liberally before sun exposure and as needed

Inactive ingredients

aloe barbadensis leaf extract, camphor, cetyl alcohol, cocoyl hydrolyzed soy protein, euphorbia cerifera (candelilla) wax, fragrance, isostearoyl hydrolyzed collagen, menthol, microcrystalline wax, olea europaea (olive) fruit oil, petrolatum, saccharin, theobroma cacao (cocoa) seed butter, thymol, tocopheryl acetate, vanillin, vitis vinifera (grape) seed oil

#34280
©2011 Blistex Inc.,
P.O. Box 5392,
Oak Brook, IL 60522-5392

PRINCIPAL DISPLAY PANEL - 7 g Container Label

NDC 10157-9539-1

Blistex®

LIP PROTECTANT/
SUNSCREEN

SPF
15

EUROPEAN FORMULA
LIP CONDITIONER™

Moisturizes & Protects For Healthy, Beautiful Lips

Enriched with Olive & Grapeseed Oils,
Vitamin E, Cocoa Butter, Lanolin and Collagen

NET WT. .25 oz (7g)